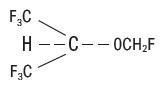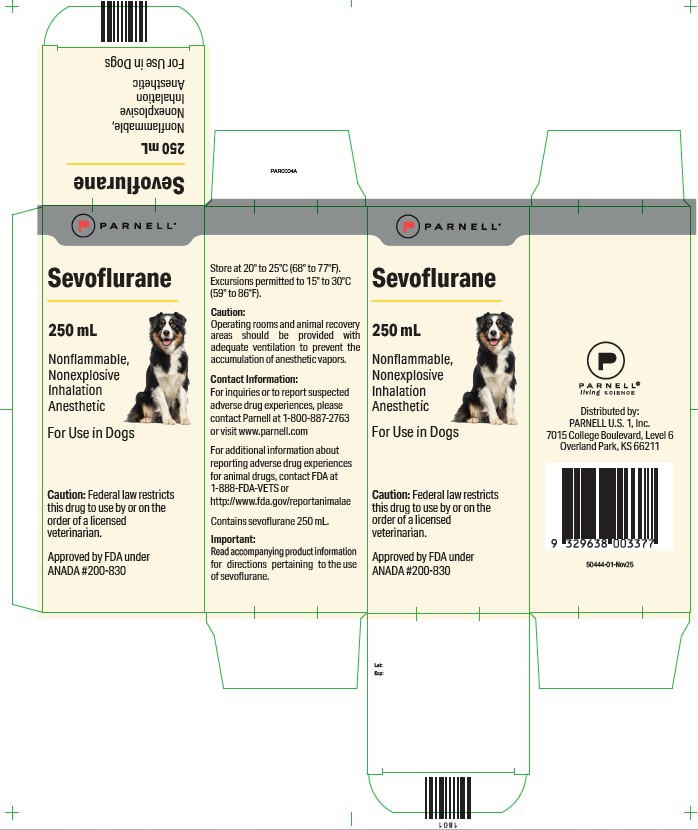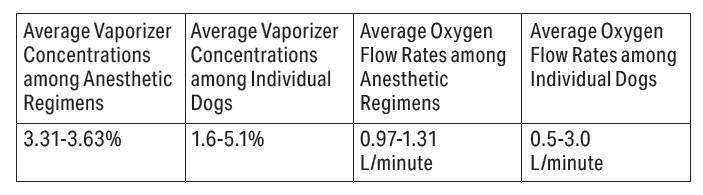 DRUG LABEL: Sevoflurane
NDC: 68504-011 | Form: LIQUID
Manufacturer: Parnell Technologies Pty Ltd
Category: animal | Type: PRESCRIPTION ANIMAL DRUG LABEL
Date: 20260219

ACTIVE INGREDIENTS: Sevoflurane 99.9 mL/250 mL

Inhalation Anesthetic For Use in Dogs

CAUTION:

Federal law restricts this drug to use by or on the order of a licensed veterinarian.

DESCRIPTION:

Sevoflurane, a volatile liquid, is a halogenated general inhalation anesthetic drug. Its chemical name is fluoromethyl 2,2,2-trifluoro-I-(trifluoromethyl) ethyl ether, and its structural formula is:

Some physical constants are:
Molecular weight ............................................................. 200.05
Boiling point at 760 mm Hg .............................................. 58.6°C
Specific gravity at 20°C ................................................. 1.520 – 1.525 g/mL
Vapor pressure in mm Hg** ................................... 20°C 157
25°C 197
36°C 317

Distribution partition coefficients at 37°C:
Blood/gas ....................................................................... 0.63 – 0.69
Water/gas ....................................................................... 0.36
Olive oil/gas ................................................................... 47 – 54
Brain/gas ........................................................................ 1.15

Mean component/gas partition coefficients at 25°C – rubber and plastic:
Conductive rubber/gas .................................................... 14.0
Butyl rubber/gas ............................................................. 7.7
Polyvinyl chloride/gas .................................................. 17.4
Polyethylene/gas ............................................................ 1.3

Sevoflurane is nonflammable and nonexplosive as defined by the requirements of International Electrotechnical Commission 601-2-13.

Sevoflurane is a clear, colorless, stable liquid containing no additives or chemical stabilizers. Sevoflurane is nonpungent. It is miscible with ethanol, ether, chloroform and petroleum benzene, and it is slightly soluble in water. Sevoflurane is stable when stored under normal room lighting condition according to instructions.

INDICATIONS:

Sevoflurane is indicated for induction and maintenance of general anesthesia in dogs.

DOSAGE AND ADMINISTRATION:

Inspired Concentration: The delivered concentration of sevoflurane should be known. Since the depth of anesthesia may be altered easily and rapidly, only vaporizers producing predictable percentage concentrations of sevoflurane should be used. Sevoflurane should be vaporized using a precision vaporizer specifically calibrated for sevoflurane. Sevoflurane contains no stabilizer. Nothing in the drug product alters calibration or operation of these vaporizers. The administration of general anesthesia must be individualized based on the patient’s response. WHEN USING SEVOFLURANE, PATIENTS SHOULD BE CONTINUOUSLY MONITORED AND FACILITIES FOR MAINTENANCE OF PATENT AIRWAY, ARTIFICIAL VENTILATION, AND OXYGEN SUPPLEMENTATION MUST BE IMMEDIATELY AVAILABLE.

Replacement of Desiccated CO₂ Absorbents: When a clinician suspects that the CO₂ absorbent may be desiccated, it should be replaced. An exothermic reaction occurs when sevoflurane is exposed to CO₂ absorbents. This reaction is increased when the CO₂ absorbent becomes desiccated (see PRECAUTIONS).

Premedication: No specific premedication is either indicated or contraindicated with sevoflurane. The necessity for and choice of premedication is left to the discretion of the veterinarian. Preanesthetic doses for premedicants may be lower than the label directions for their use as a single medication.¹

Induction: For mask induction using sevoflurane alone, inspired concentrations of up to 7% sevoflurane with oxygen are employed to induce surgical anesthesia in the healthy dog. These concentrations can be expected to produce surgical anesthesia in 3 to 14 minutes. Due to the rapid and dose dependent changes in anesthetic depth, care should be taken to prevent overdosing. Respiration must be monitored closely in the dog and supported when necessary with supplemental oxygen and/or assisted ventilation.

Maintenance: Sevoflurane may be used for maintenance anesthesia following mask induction using sevoflurane or following injectable induction agents. The concentration of vapor necessary to maintain anesthesia is much less than that required to induce it.

Surgical levels of anesthesia in the healthy dog may be maintained with inhaled concentrations of 3.7–4.0% sevoflurane in oxygen in the absence of premedication and 3.3–3.6% in the presence of premedication. The use of injectable induction agents without premedication has little effect on the concentrations of sevoflurane required for maintenance. Anesthetic regimens that include opioid, alpha₂-agonist, benzodiazepine or phenothiazine premedication will allow the use of lower sevoflurane maintenance concentrations.

CONTRAINDICATIONS:

Sevoflurane is contraindicated in dogs with a known sensitivity to sevoflurane or other halogenated agents.

WARNINGS:

Sevoflurane is a profound respiratory depressant. DUE TO THE RAPID AND DOSE DEPENDENT CHANGES IN ANESTHETIC DEPTH, RESPIRATION MUST BE MONITORED CLOSELY IN THE DOG AND SUPPORTED WHEN NECESSARY WITH SUPPLEMENTAL OXYGEN AND/OR ASSISTED VENTILATION.

In cases of severe cardiopulmonary depression, discontinue drug administration, ensure the existence of a patent airway and initiate assisted or controlled ventilation with pure oxygen. Cardiovascular depression should be treated with plasma expanders, pressor agents, antiarrhythmic agents or other techniques as appropriate for the observed abnormality. Due to sevoflurane’s low solubility in blood, increasing the concentration may result in rapid changes in anesthetic depth and hemodynamic changes (dose dependent decreases in respiratory rate and blood pressure) compared to other volatile anesthetics. Excessive decreases in blood pressure or respiratory depression may be corrected by decreasing or discontinuing the inspired concentration of sevoflurane. Potassium hydroxide containing CO2 absorbents (e.g. BARALYME®) are not
recommended for use with sevoflurane.

ADVERSE REACTIONS:

The most frequently reported adverse reactions during maintenance anesthesia were hypotension, followed by tachypnea, muscle tenseness, excitation, apnea, muscle fasciculations and emesis.

Infrequent adverse reactions include paddling, retching, salivation, cyanosis, premature ventricular contractions and excessive cardiopulmonary depression.

Transient elevations in liver function tests and white blood cell count may occur with sevoflurane, as with the use of other halogenated anesthetic agents.

PRECAUTIONS:

Halogenated volatile anesthetics can react with desiccated carbon dioxide (CO2) absorbents to produce carbon monoxide (CO) that may result in elevated carboxyhemoglobin levels in some patients. To prevent this reaction, sevoflurane should not be passed through desiccated soda lime or barium hydroxide lime.

Replacement of Desiccated CO2 Absorbents:When a clinician suspects that the CO2 absorbent may be desiccated, it should be replaced before administration of sevoflurane. The exothermic reaction that occurs with sevoflurane and CO2 absorbents is increased when the CO2 absorbent becomes desiccated, such as after an extended period of dry gas flow through the CO2 absorbent canisters. Extremely rare cases of spontaneous fire in the respiratory circuit of the anesthesia machine have been reported during sevoflurane use in conjunction with the use of a desiccated CO2 absorbent, specifically those containing potassium hydroxide (e.g.BARALYME®). Potassium hydroxide containing CO2 absorbents are not recommended for use with sevoflurane. An unusually delayed rise in the inspired gas concentration (decreased delivery) of sevoflurane compared with the vaporizer setting may indicate excessive heating of the CO2 absorbent canister and chemical breakdown of sevoflurane. The color indicator of most CO2 absorbent may not change upon desiccation. Therefore, the lack of significant color change should not be taken as an
assurance of adequate hydration. CO2 absorbents should be replaced routinely regardless of the state of the color indicator.

The use of some anesthetic regimens that include sevoflurane may result in bradycardia that is reversible with anticholinergics. Studies using sevoflurane anesthetic regimens that included atropine or glycopyrrolate as premedicants showed these anticholinergics to be compatible with sevoflurane in dogs.

During the induction and maintenance of anesthesia, increasing the concentration of sevoflurane produces dose dependent decreases in blood pressure and respiratory rate. Due to sevoflurane’s low solubility in blood, these changes may occur more rapidly than with other volatile anesthetics. Excessive decreases in blood pressure or respiratory depression may be related to depth of anesthesia and may be corrected
by decreasing the inspired concentration of sevoflurane. RESPIRATION MUST BE MONITORED CLOSELY IN THE DOG AND SUPPORTED WHEN NECESSARY WITH SUPPLEMENTAL OXYGEN AND/OR ASSISTED VENTILATION. The low solubility of sevoflurane also facilitates rapid elimination by the lungs.

The use of sevoflurane in humans increases both the intensity and duration of neuromuscular blockade induced by nondepolarizing muscle relaxants. The use of sevoflurane with nondepolarizing muscle relaxants has not been evaluated in dogs.

Compromised or debilitated dogs: Doses may need adjustment for geriatric or debilitated dogs. Because clinical experience in administering sevoflurane to dogs with renal, hepatic and cardiovascular insufficiency is limited, its safety in these dogs has not been established.

Breeding dogs: The safety of sevoflurane in dogs used for breeding purposes, during pregnancy, or in lactating bitches, has not been evaluated.

Neonates: The safety of sevoflurane in young dogs (less than 12 weeks of age) has not been evaluated.

HUMAN SAFETY:

Not for human use. Keep out of reach of children.

Operating rooms and animal recovery areas should be provided with adequate ventilation to prevent the accumulation of anesthetic vapors.

There is no specific work exposure limit established for sevoflurane. However, the National Institute for Occupational Safety and Health has recommended an 8 hour time-weighted average limit of 2 ppm for halogenated anesthetic agents in general.

Direct exposure to eyes may result in mild irritation. If eye exposure occurs, flush with plenty of water for 15 minutes. Seek medical attention if irritation persists.

Symptoms of human overexposure (inhalation) to sevoflurane vapors include respiratory depression, hypotension, bradycardia, shivering, nausea and headache. If these symptoms occur, remove the individual from the source of exposure and seek medical attention.

To report suspected adverse events, for technical assistance or to obtain a copy of the Safety Data Sheet(s), contact Parnell at 1-800-887-2763 or visit www.parnell.com.

For additional information about adverse drug experience reporting for animal drugs, contact FDA at 1-888-FDA-VETS or online at www.fda.gov/reportanimalae.

CLINICAL PHARMACOLOGY:

Sevoflurane is an inhalational anesthetic agent for induction and maintenance of general anesthesia. The Minimum Alveolar Concentration (MAC) of sevoflurane as determined in 18 dogs is 2.36%.^2 MAC is defined as that alveolar concentration at which 50% of healthy patients fail to respond to noxious stimuli. Multiples of MAC are used as a guide for surgical levels of anesthesia, which are typically 1.3 to 1.5 times the MAC value.

Because of the low solubility of sevoflurane in blood (blood/gas partition coefficient at 37ºC = 0.63 - 0.69), a minimal amount of sevoflurane is required to be dissolved in the blood before the alveolar partial pressure is in equilibrium with the arterial partial pressure. During sevoflurane induction, there is a rapid increase in alveolar concentration toward the inspired concentration.

Sevoflurane produces only modest increases in cerebral blood flow and metabolic rate, and has little or no ability to potentiate seizures.^3 Sevoflurane has a variable effect on heart rate, producing increases or decreases depending on experimental conditions.^4,5 Sevoflurane produces dose-dependent decreases in mean arterial pressure, cardiac output and myocardial contraction.^6 Among inhalation anesthetics, sevoflurane has low arrhythmogenic potential.^7

Sevoflurane is chemically stable. No discernible degradation occurs in the presence of strong acids or heat. Sevoflurane reacts through direct contact with CO2 absorbents (soda lime and barium hydroxide lime) producing pentafluoroisopropenyl fluoromethyl ether (PIFE, C4H2F6O), also known as Compound A, and trace amounts of pentafluoromethoxy isopropyl fluoromethyl ether (PMFE, C5H6F6O), also known as Compound B.

Compound A:
The production of degradants in the anesthesia circuit results from the extraction of the acidic proton in the presence of a strong base (potassium hydroxide and/or NaOH) forming an alkene (Compound A) from sevoflurane.

Compound A is produced when sevoflurane interacts with soda lime or barium hydroxide lime. Reaction with barium hydroxide lime results in a greater production of Compound A than does reaction with soda lime. Its concentration in a circle absorber system increases with increasing sevoflurane concentrations and with decreasing fresh gas flow rates. Sevoflurane degradation in soda lime has been shown to increase with temperature. Since the reaction of carbon dioxide with absorbents is exothermic, this temperature increase will be determined by the quantities of CO2 absorbed, which in turn will depend on fresh gas flow in the anesthetic circle system, metabolic status of the patient and ventilation. Although Compound A is a dose-dependent nephrotoxin in rats, the mechanism of this renal toxicity is unknown. Two spontaneously breathing dogs under sevoflurane anesthesia showed increases in concentrations of Compound A as the oxygen flow rate was decreased at hourly intervals, from 500 mL/min (36 and 18 ppm Compound A) to 250 mL/min in (43 and 31 ppm) to 50 mL/min (61 and 48 ppm).^8

Fluoride ion metabolite:
Sevoflurane is metabolized to hexafluoroisopropanol (HFIP) with release of inorganic fluoride and CO2. Fluoride ion concentrations are influenced by the duration of anesthesia and the concentration of sevoflurane. Once formed, HFIP is rapidly conjugated with glucuronic acid and eliminated as a urinary metabolite. No other metabolic pathways for sevoflurane have been identified. In humans, the fluoride ion half-life was prolonged in patients with renal impairment, but human clinical trials contained no reports of toxicity associated with elevated fluoride ion levels. In a study in which 4 dogs were exposed to 4% sevoflurane for 3 hours, maximum serum fluoride concentrations of 17.0 - 27.0 mmole/L were observed after 3 hours of anesthesia. Serum fluoride fell quickly after anesthesia ended, and had returned to baseline by 24 hours post-anesthesia.
In a safety study, eight healthy dogs were exposed to sevoflurane for 3 hours/day, 5 days/week for 2 weeks (total 30 hours exposure) at a flow rate of 500 mL/min in a semi-closed, rebreathing system with soda lime. Renal toxicity was not observed in the study evaluation of clinical signs, hematology, serum chemistry, urinalysis, or gross or microscopic pathology.

DRUG INTERACTIONS:

In the clinical trial, sevoflurane was used safely in dogs that received frequently used veterinary products including steroids and heartworm and flea preventative products.

Intravenous Anesthetics: Sevoflurane administration is compatible with barbiturates, propofol and other commonly used intravenous anesthetics.

Benzodiazepines and Opioids: Benzodiazepines and opioids would be expected to decrease the MAC of sevoflurane in the same manner as other inhalational anesthetics. Sevoflurane is compatible with benzodiazepines and opioids as commonly used in surgical practice.

Phenothiazines and Alpha₂-Agonists: Sevoflurane is compatible with phenothiazines and alpha₂- agonists as commonly used in surgical practice.

In a laboratory study, the use of the acepromazine/oxymorphone/thiopental/sevoflurane anesthetic regimen resulted in prolonged recoveries in eight (of 8) dogs compared to recoveries from sevoflurane alone.

CLINICAL PHARMACOLOGY:

The effectiveness of sevoflurane was investigated in a clinical study involving 196 dogs. Thirty dogs were mask-induced with sevoflurane using anesthetic regimens that included various premedicants. During the clinical study, one hundred sixty-six dogs received sevoflurane maintenance anesthesia as part of several anesthetic regimens that used injectable induction agents and various premedicants.

The duration of anesthesia and the choice of anesthetic regimens were dependent upon the procedures that were performed. Duration of anesthesia ranged from 16 to 424 minutes among the individual dogs. Sevoflurane vaporizer concentrations during the first 30 minutes of maintenance anesthesia were similar among the various anesthetic regimens. The quality of maintenance anesthesia was considered good or excellent in 169 out of 196 dogs.

The table shows the average vaporizer concentrations and oxygen flow rates during the first 30 minutes for all sevoflurane maintenance anesthesia regimens:

During the clinical trial, when a barbiturate was used for induction, the times to extubation, sternal recumbency and standing recovery were longer for dogs that received anesthetic regimens containing two preanesthetics compared to regimens containing one preanesthetic. Recovery times were shorter when anesthetic regimens used sevoflurane or propofol for induction. The quality of recovery was considered good or excellent in 184 out of 196 dogs.

Anesthetic regimen drug dosages, physiological responses, and the quality of induction, maintenance and recovery were comparable between 10 sighthounds and other breeds evaluated in the study. During the clinical study there was no indication of prolonged recovery times in the sighthounds.

HOW SUPPLIED:

Sevoflurane is supplied in 250 mL amber colored bottles.

STORAGE CONDITIONS:

Store at 20° to 25°C (68° to 77°F). Excursions permitted to 15° to 30°C (59° to 86°F).

REFERENCES:

1. Plumb, D.C. (ed.). Veterinary Drug Handbook. 2nd Edition. University of Iowa Press, Ames, IA; p. 424 (1995).

2. Kazama, T. and Ikeda, K. Comparison of MAC and the rate of rise of alveolar concentration of sevoflurane with halothane and isoflurane in the dog. Anesthesiology. 68: 435–437 (1988).

3. Scheller, M.S., Nakakimura, K., Fleischer, J.E. and Zornow, M.H. Cerebral effects of sevoflurane in the dog: Comparison with isoflurane and enflurane. Br. J. Anesthesia. 65: 388–392 (1990).

4. Frink, E.J., Morgan, S.E., Coetzee, A., Conzen, P.F. and Brown, B.R. Effects of sevoflurane, halothane, enflurane and isoflurane on hepatic blood flow and oxygenation in chronically instrumented greyhound dogs. Anesthesiology. 76: 85–90 (1992).

5. Kazama, T. and Ikeda, K. The comparative cardiovascular effects of sevoflurane with halothane and isoflurane. J. Anesthesiology. 2: 63–8 (1988).

6. Bernard, J.M., Wouters, P.F., Doursout, M.F., Florence, B., Chelly, J.E. and Merin, R.G. Effects of sevoflurane on cardiac and coronary dynamics in chronically instrumented dogs. Anesthesiology. 72: 659–662 (1990).

7. Hayaski, Y., Sumikawa, K., Tashiro, C., Yamatodani, A. and Yoshiya, I. Arrhythmogenic threshold of epinephrine during sevoflurane, enflurane and isoflurane anesthesia in dogs. Anesthesiology. 69: 145–147 (1988).

8. Muir, W.W. and Gadawski, J. Cardiorespiratory effects of low-flow and closed circuit inhalation anesthesia, using sevoflurane delivered with an in-circuit vaporizer and concentrations of Compound A. Am. J. Vet. Res. 59(5): 603–608 (1998).

Approved by FDA under ANADA #200-830

Contact Information:
For inquiries or to report suspected adverse drug experiences, please contact Parnell at 1-800-887-2763 or visit www.parnell.com

For additional information about reporting adverse drug experiences for animal drugs, contact FDA at 1-888-FDA-VETS or http://www.fda.gov/reportanimalae

Distributed by: PARNELL U.S. 1, Inc.
7015 College Boulevard, Level 6,
Overland Park, KS 66211

50445-01-Nov25
PAR0006A

Image of 250 mL Carton

Sevoflurane

250 mL

Nonflammable, Nonexplosive Inhalation Anesthetic

FOR USE IN HORSES AND DOGS

Caution: Federal law restricts this drug to use by or on the order of a licensed veterinarian.

Approved by FDA under ANADA # 200-830